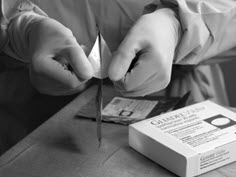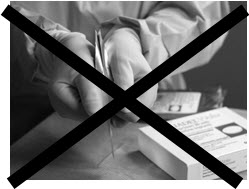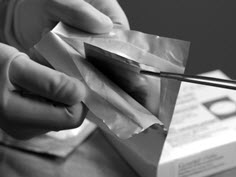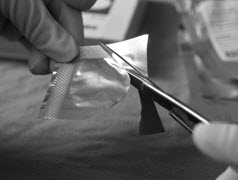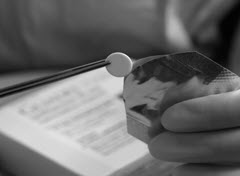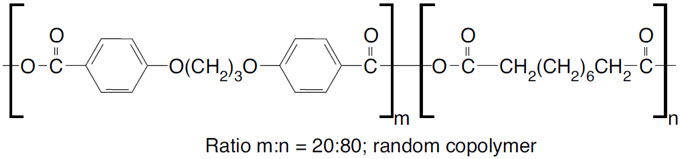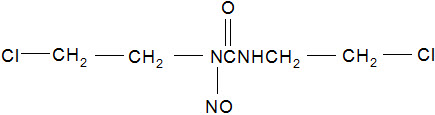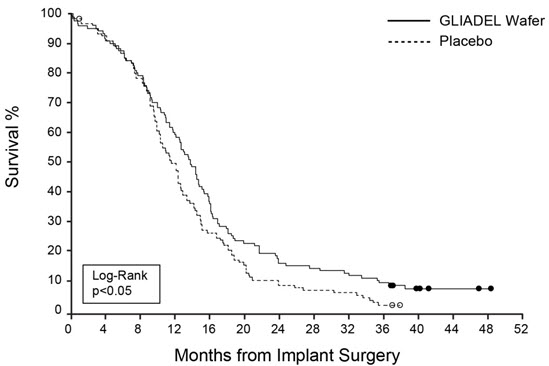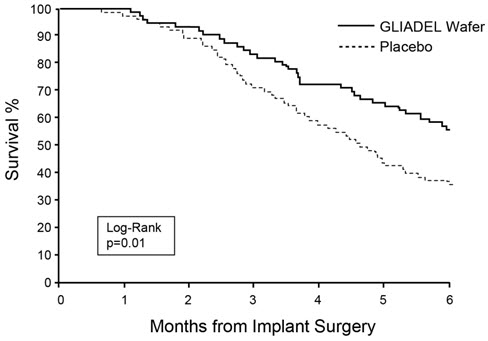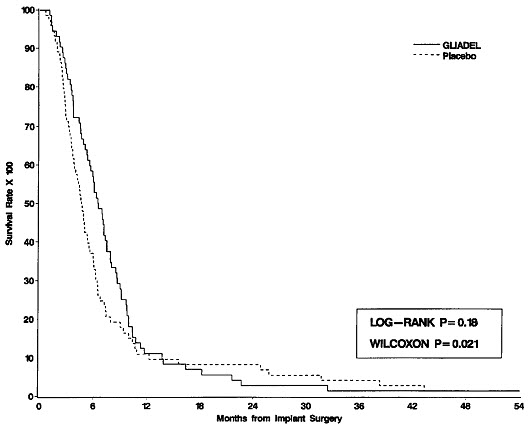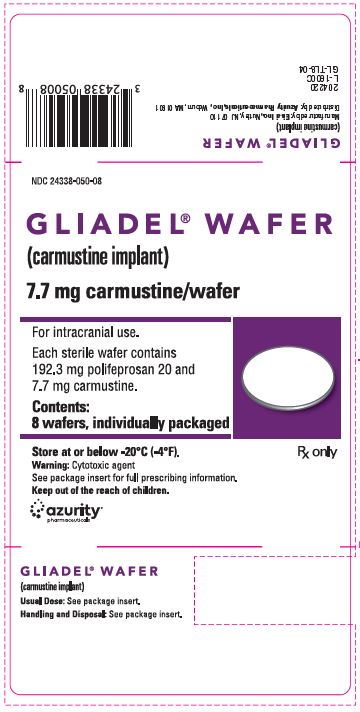 DRUG LABEL: Gliadel
NDC: 24338-050 | Form: WAFER
Manufacturer: Azurity Pharmaceuticals, Inc.
Category: prescription | Type: HUMAN PRESCRIPTION DRUG LABEL
Date: 20241205

ACTIVE INGREDIENTS: CARMUSTINE 7.7 mg/1 1
INACTIVE INGREDIENTS: POLIFEPROSAN 20

HIGHLIGHTS OF PRESCRIBING INFORMATION

These highlights do not include all the information needed to use GLIADEL WAFER safely and effectively. See full prescribing information for GLIADEL WAFER.
GLIADEL® WAFER (carmustine implant), for intracranial use
Initial U.S. Approval: 1996

1 INDICATIONS AND USAGE

GLIADEL Wafer is an alkylating drug indicated for the treatment of:

- newly-diagnosed high-grade glioma as an adjunct to surgery and radiation (1) and
- recurrent glioblastoma as an adjunct to surgery (1)

2 DOSAGE AND ADMINISTRATION

- Recommended dose: Eight 7.7 mg wafers (61.6 mg total dose) implanted intracranially (2.1, 2.2)
- Follow preparation and handling recommendations (2.3).

3 DOSAGE FORMS AND STRENGTHS

- Each GLIADEL Wafer contains 7.7 mg of carmustine (3).

4 CONTRAINDICATIONS

None (4)

5 WARNINGS AND PRECAUTIONS

- Seizures: Monitor patients for seizures following implantation (5.1).
- Intracranial hypertension: Monitor patients for signs of increased intracranial pressure (5.2).
- Impaired neurosurgical wound healing: Monitor patients for complications of craniotomy (5.3).
- Meningitis: Monitor patients for signs of bacterial or chemical meningitis (5.4).
- Wafer migration: Monitor patients for signs of obstructive hydrocephalus (5.5).
- Embryo-fetal toxicity: Can cause fetal harm. Advise patients of the potential risk to a fetus. Advise males and females of reproductive potential to use an effective method of contraception. (5.6, 8.1, 8.3).

6 ADVERSE REACTIONS

- Newly-Diagnosed High-Grade Glioma: Most common adverse reactions (incidence >10% and between arm difference ≥4%) are cerebral edema, asthenia, nausea, vomiting, constipation, wound healing abnormalities and depression (6.1).
- Recurrent High-Grade Glioma: Most common adverse reactions (incidence >10% and between arm difference ≥4%) are urinary tract infection, wound healing abnormalities and fever (6.1).

To report SUSPECTED ADVERSE REACTIONS, contact Azurity Pharmaceuticals, Inc. at 1-800-461-7449 or FDA at 1-800-FDA-1088 orwww.fda.gov/medwatch .

8 USE IN SPECIFIC POPULATIONS

- Lactation: Advise not to breastfeed (8.2).

FULL PRESCRIBING INFORMATION

1 INDICATIONS AND USAGE

GLIADEL Wafer is indicated for the treatment of patients with:

- newly-diagnosed high-grade glioma as an adjunct to surgery and radiation, and
- recurrent glioblastoma as an adjunct to surgery.

2 DOSAGE AND ADMINISTRATION

2.1 Recommended Dose

The recommended dose of GLIADEL Wafer is eight 7.7 mg wafers for a total of 61.6 mg implanted intracranially. The safety and effectiveness of repeat administration have not been studied.

2.2 Insertion Instructions

Following maximal tumor resection, confirmation of tumor pathology and establishment of hemostasis, place up to a maximum of eight GLIADEL Wafers to cover as much of the resection cavity as possible. Should the size and shape of the resected cavity not accommodate eight wafers, place the maximum number of wafers feasible within the cavity. Slight overlapping of the wafers is acceptable. Wafers broken in half may be used, but discard wafers broken in more than two pieces. Oxidized regenerated cellulose (Surgicel®) may be placed over the wafers to secure them against the cavity surface. After placement of the wafers, irrigate the resection cavity and close the dura in a water-tight fashion.

2.3 Preparation and Safe Handling

GLIADEL Wafers contain a cytotoxic drug. Follow applicable special handling and disposal procedures.^1

Each wafer is packaged within two nested aluminum foil laminate pouches. The inner pouch is sterile and is designed to maintain product sterility and protect the product from moisture. The outside surface of the outer laminated aluminum foil pouch is a peelable overwrap and is not sterile.

Deliver GLIADEL Wafers to the operating room in their outer aluminum foil pouch, unopened. Do not open the pouch until the wafers are ready to be implanted .GLIADEL Wafers in unopened outer foil pouches are stable at room temperature for six hours at a time for up to three cycles within a 30-day period.

Exposure to carmustine can cause severe burning and hyperpigmentation of the skin. Use double gloves when handling GLIADEL Wafers. Discard the outer gloves into a biohazard waste container after use. Use a dedicated surgical instrument for wafer implantation. If repeat neurosurgical intervention is indicated, handle residual wafers or wafer remnants as potential cytotoxic agents.

Instructions for Opening Pouch Containing GLIADEL Wafer

Read all steps of the instructions prior to opening the pouch.

Instructions for opening the pouch containing GLIADEL Wafer can be viewed at the following website: http://gliadel.com/hcp/pouch-opening-instructions. Illustrations are also pictured below.

Figure 1:To remove the sterile inner pouch from the outer pouch, locate the folded corner and slowly pull in an outward motion.

Figure 2:Do NOT pull in a downward motion rolling knuckles over the pouch. This may exert pressure on the wafer and cause it to break.

Figure 3:The inner pouch is a multi-layered, silver colored, foil laminate. Remove the inner pouch by grabbing hold of the crimped edge of the inner pouch using a sterile instrument and pulling upward.

Figure 4:To open the inner pouch, gently hold the crimped edge and cut in an arc-like fashion around the wafer.

Figure 5:To remove the GLIADEL Wafer, gently grasp the wafer with the aid of forceps and place it onto a designated sterile field.

3 DOSAGE FORMS AND STRENGTHS

GLIADEL Wafer is an off-white to pale yellow round wafer. Each GLIADEL Wafer contains 7.7 mg of carmustine.

4 CONTRAINDICATIONS

None.

5 WARNINGS AND PRECAUTIONS

5.1 Seizures

Seizures occurred in 37% of patients treated with GLIADEL Wafers for recurrent glioma in Study 2. New or worsening (treatment emergent) seizures occurred in 20% of patients; 54% of treatment emergent seizures occurred within the first 5 post-operative days [see Adverse Reactions (6.1)]. The median time to onset of the first new or worsened post-operative seizure was four days. Institute optimal anti-seizure therapy prior to surgery. Monitor patients for seizures postoperatively.

5.2 Intracranial Hypertension

Brain edema occurred in 23% of patients with newly diagnosed glioma treated with GLIADEL Wafers in Study 1. Additionally, one GLIADEL-treated patient experienced intracerebral mass effect unresponsive to corticosteroids which led to brain herniation [see Adverse Reactions (6.1)] . Monitor patients closely for intracranial hypertension related to brain edema, inflammation, or necrosis of the brain tissue surrounding the resection. In refractory cases, consider re-operation and removal of GLIADEL Wafers or Wafer remnants.

5.3 Impaired Neurosurgical Wound Healing

Impaired neurosurgical wound healing including wound dehiscence, delayed wound healing, and subdural, subgaleal, or wound effusions occur with GLIADEL Wafer treatment. In Study 1, 16% of GLIADEL Wafer-treated patients with newly diagnosed glioma experienced impaired intracranial wound healing and 5% had cerebrospinal fluid leaks. In Study 2, 14% of GLIADEL Wafer-treated patients with recurrent high-grade glioma experienced wound healing abnormalities [see Adverse Reactions (6.1)]. Monitor patients post-operatively for impaired neurosurgical wound healing.

5.4 Meningitis

Meningitis occurred in 4% of patients with recurrent glioma receiving GLIADEL Wafers in Study 2. Two cases of meningitis were bacterial; one patient required removal of the Wafers four days after implantation; the other developed meningitis following reoperation for recurrent tumor. One case was diagnosed as chemical meningitis and resolved following steroid treatment. In one case the cause was unspecified, but meningitis resolved following antibiotic treatment. Monitor postoperatively for signs of meningitis and central nervous system infection.

5.5 Wafer Migration

GLIADEL Wafer migration can occur. To reduce the risk of obstructive hydrocephalus due to wafer migration into the ventricular system, close any communication larger than the diameter of a Wafer between the surgical resection cavity and the ventricular system prior to Wafer implantation. Monitor patients for signs of obstructive hydrocephalus.

5.6 Embryo-Fetal Toxicity

GLIADEL Wafers can cause fetal harm when administered to a pregnant woman. Carmustine, the active component of GLIADEL Wafer, is embryotoxic and teratogenic in rats at exposures less than the exposure at the recommended human dose based on body surface area (BSA) and embryotoxic in rabbits at exposures similar to the exposure at the recommended human dose based on BSA.

Advise patients of the potential risk to a fetus. Advise females of reproductive potential to use effective contraception for 6 months after implantation of GLIADEL Wafer. Advise males with female partners of reproductive potential to use effective contraception for 3 months following implantation of GLIADEL Wafers [see Use in Specific Populations (8.1, 8.3), Nonclinical Toxicology (13.1)].

6 ADVERSE REACTIONS

The following serious adverse reactions are discussed elsewhere in the labeling:

- Seizures [see Warnings and Precautions (5.1)]
- Intracranial Hypertension [see Warnings and Precautions (5.2)]
- Impaired Neurosurgical Wound Healing [see Warnings and Precautions (5.3)]
- Meningitis [see Warnings and Precautions (5.4)]

6.1 Clinical Trials Experience

Because clinical trials are conducted under widely varying conditions, adverse reaction rates observed in the clinical trials of a drug cannot be directly compared to rates in the clinical trials of another drug and may not reflect the rates observed in practice.

Newly-Diagnosed High-Grade Glioma

The safety of GLIADEL Wafers was evaluated in a multicenter, randomized (1:1), double-blind, placebo controlled trial of 240 adult patients with newly-diagnosed high-grade glioma who received up to eight GLIADEL Wafers or matched placebo implanted against the resection surfaces after maximal tumor resection (Study 1).

The population in Study 1 was 67% male and 97% White, and the median age was 53 years (range: 21-72). Eighty-seven percent had a Karnofsky performance status ≥ 70 and 71% had a Karnofsky performance status of ≥ 80%. Seventy-eight percent had a histologic subtype of glioblastoma as determined by central pathology review. Thirty-eight percent of patients received 8 wafers and 78% received ≥ 6 wafers. Starting three weeks after surgery, 80% of patients received standard limited field radiation therapy (RT) described as 55-60 Gy delivered in 28 to 30 fractions over six weeks; an additional 11% received no radiotherapy and the remainder received non-standard radiotherapy or a combination of standard and non-standard radiotherapy. At the time of progression, 12% received systemic chemotherapy.

Deaths occurred within 30 days of wafer implantation in 5 (4%) of patients receiving GLIADEL Wafers compared to 2 (2%) of patients receiving placebo. Deaths on the GLIADEL arm resulted from cerebral hematoma/edema (n=3), pulmonary embolism (n=1) and acute coronary event (n=1). Deaths on the placebo arm resulted from sepsis (n=1) and malignant disease (n=1).

The incidence of common adverse reactions in GLIADEL Wafer-treated patients is listed in Table 1. The incidence of local adverse reactions is shown in Table 2.

Table 1. Per-Patient Incidence of Adverse Reactions Occurring in Gliadel Wafer-Treated Patients with Newly-Diagnosed High-Grade Glioma (Study 1) (Between Arm Difference of ≥ 4%)
Adverse Reaction | GLIADEL Wafer N=120 | Placebo N=120
Adverse Reaction | % | %
GASTROINTESTINAL
Nausea | 22 | 17
Vomiting | 21 | 16
Constipation | 19 | 12
Abdominal pain | 8 | 2
GENERAL AND ADMINISTRATION SITE CONDITION
Asthenia | 22 | 15
Chest pain | 5 | 0
INJURY, POISONING AND PROCEDURAL COMPLICATIONS
Wound healing abnormalities [Included (1) fluid, CDS, or subdural fluid collection; (2) CSF leak; (3) wound dehiscence, breakdown, or poor healing; and (4) subgaleal or wound effusions (including yellow discharge at the incision)] | 16 | 12
MUSCULOSKELETAL AND CONNECTIVE TISSUE
Back pain | 7 | 3
PSYCHIATRIC
Depression | 16 | 10

Table 2. Incidence of Local Adverse Reactions, Study 1 [Not seen at baseline or worsened if present at baseline.]
Local Adverse Reactions | GLIADEL Wafer N=120 | Placebo N=120
Local Adverse Reactions | % | %
Cerebral edema | 23 | 19
Intracranial hypertension | 9 | 2
Cerebral hemorrhage | 6 | 4
Brain abscess | 6 | 4
Brain cyst | 2 | 3

Recurrent High-Grade Glioma

The safety of GLIADEL Wafers was evaluated in a multicenter, randomized (1:1), double-blind, placebo controlled trial of 222 patients with recurrent high-grade glioma who received up to eight GLIADEL Wafers or matched placebo implanted against the resection surfaces after maximal tumor resection (Study 2). Patients were required to have had prior definitive external beam radiation therapy sufficient to disqualify them from additional radiation therapy. All patients were eligible to receive chemotherapy which was withheld at least four weeks (six weeks for nitrosoureas) prior to and two weeks after surgery.

The population in Study 2 was 64% male, 92% White, and the median age was 49 years (range: 19-80). Sixty-five percent had a histologic subtype of glioblastoma, 26% had anaplastic astrocytoma or another anaplastic variant, 73% had a Karnofsky performance status ≥ 70, 53% had a Karnofsky performance status of ≥ 80%, 73% had only one prior surgery, and 46% had prior treatment with nitrosourea. Eighty-one percent of patients received 8 wafers and 96% received ≥ 6 wafers.

Sixty-four severe adverse reactions were reported in 43(39%) patients receiving GLIADEL Wafers. Adverse reactions in GLIADEL Wafer-treated patients are shown in Table 3. Meningitis occurred in four patients receiving GLIADEL Wafers and in no patients receiving placebo. Bacterial meningitis was confirmed in two patients: the first with onset four days following GLIADEL Wafer implantation; the second following resection for tumor recurrence 155 days following GLIADEL Wafer implantation. One case, attributed to chemical meningitis resolved following steroid treatment. The cause of the fourth case was undetermined but resolved following antibiotic treatment.

Table 3. Per-Patient Incidence of Adverse Reactions in Gliadel Wafer-Treated Patients with Recurrent High-Grade Glioma (Study 2) (Between Arm Difference of ≥ 4%)
Adverse Reaction | GLIADEL Wafer N=110 | Placebo N=112
Adverse Reaction | % | %
GENERAL
Fever | 12 | 8
INFECTIOUS
Urinary tract infections | 21 | 17
INJURY, POISONING AND PROCEDURAL COMPLICATIONS
Wound healing abnormalities [Included (1) fluid, CDS, or subdural fluid collection; (2) CSF leak; (3) wound dehiscence, breakdown, or poor healing; and (4) subgaleal or wound effusions (including yellow discharge at the incision)] | 14 | 5

The incidence of seizures is shown in Table 4. The incidence of hydrocephalus, cerebral edema and intracranial hypertension is shown in Table 5.

Table 4. Incidence of Seizures, Study 2
Adverse Reaction | GLIADEL Wafer N=110 | Placebo N=112
Adverse Reaction | Patients with seizures (%)
Any seizures after wafer implantation | 37 | 29
New or worsening seizures | 20 | 20
Time to new or worsening seizures (days) [Days from implantation to onset of first new or worsening seizure.]
Mean (SD) | 26.09 (0.75) | 62.36 (48.66)
Median | 3.5 | 61.0

Table 5. Hydrocephalus and Cerebral Edema, Study 2 [Not seen at baseline or worsened if present at baseline.]
Adverse Reaction | GLIADEL Wafer N=110 | Placebo N=112
Adverse Reaction | % | %
Hydrocephalus | 5 | 2
Cerebral edema | 4 | 1

8 USE IN SPECIFIC POPULATIONS

8.1 Pregnancy

Risk Summary

GLIADEL Wafer can cause fetal harm when administered to a pregnant woman. There are no available data on GLIADEL use in pregnant women. There have been no animal reproductive studies with GLIADEL Wafer; however, carmustine, the active component of GLIADEL Wafer, is embryotoxic and teratogenic in rats at exposures less than the exposure at the recommended human dose based on body surface area (BSA) and embryotoxic in rabbits at exposures similar to exposures at the recommended human dose based on BSA (see Data) . Advise pregnant women of the potential risk to a fetus.

In the U.S. general population, the estimated background risk of major birth defects and miscarriage in clinically recognized pregnancies is 2% to 4% and 15% to 20%, respectively.

Data

Animal Data

There are no studies assessing the reproductive toxicity of GLIADEL Wafer; however, carmustine, the active component of GLIADEL Wafer, is embryotoxic and teratogenic in rats at intraperitoneal doses of 0.5 mg/kg/day or greater when given on gestation days 6 through 15. Carmustine caused fetal malformations (anophthalmia, micrognathia, omphalocele) at 1 mg/kg/day (about 0.12 times the recommended human dose, eight wafers of 7.7 mg carmustine/wafer, based on BSA). Carmustine was embryotoxic in rabbits at intravenous doses of 4 mg/kg/day (about 1.2 times the recommended human dose based on BSA). Embryotoxicity was characterized by increased embryo-fetal deaths, reduced numbers of litters, and reduced litter sizes.

8.2 Lactation

Risk Summary

No data are available regarding the presence of carmustine, the active component of GLIADEL Wafer, or its metabolites in human milk or its effects on the breastfed child or on milk production. Because of the potential for serious adverse reactions in breastfed children from GLIADEL Wafers, advise women not to breastfeed following implantation with GLIADEL Wafers and for at least 7 days after implantation.

8.3 Females and Males of Reproductive Potential

Pregnancy Testing

Verify pregnancy status of females of reproductive potential prior to implantation with GLIADEL Wafer [see Use in Specific Populations (8.1)].

Contraception

GLIADEL Wafer can cause fetal harm when administered to a pregnant woman [see Use in Specific Populations (8.1)] .

Females Advise females of reproductive potential to use effective contraception for 6 months after implantation of GLIADEL Wafer.

Males

Based on its mechanism of action, advise males with female partners of reproductive potential to use effective contraception for 3 months following implantation of GLIADEL Wafer [see Clinical Pharmacology (12.1), Nonclinical Toxicology (13.1)].

Infertility

Males

Carmustine caused testicular degeneration in animals. Advise male patients of the potential risk of infertility [see Nonclinical Toxicology (13.1)] .

8.4 Pediatric Use

The safety and effectiveness of GLIADEL Wafer in pediatric patients have not been established.

8.5 Geriatric Use

Clinical trials of GLIADEL Wafer did not include sufficient numbers of patients aged 65 years and over to determine whether they respond differently from younger patients.

11 DESCRIPTION

GLIADEL Wafer is an implant for intracranial use, containing carmustine, a nitrosourea alkylating agent, and polifeprosan, a biodegradable copolymer used to control the release of carmustine. It is a sterile, off-white to pale yellow wafer approximately 1.45 cm in diameter and 1 mm thick. Each wafer contains 7.7 mg of carmustine [1, 3-bis (2-chloroethyl)-1-nitrosourea, or BCNU] and 192.3 mg of a biodegradable polyanhydride copolymer. The copolymer, polifeprosan 20, consists of poly [bis (p-carboxyphenoxy)] propane and sebacic acid in a 20:80 molar ratio. Carmustine is homogeneously distributed in the copolymer matrix.

The structural formula for polifeprosan 20 is:

The structural formula for carmustine is:

12 CLINICAL PHARMACOLOGY

12.1 Mechanism of Action

The activity of GLIADEL Wafer is due to release of cytotoxic concentrations of carmustine, a DNA and RNA alkylating agent, into the tumor resection cavity. On exposure to the aqueous environment of the resection cavity, the anhydride bonds in the copolymer are hydrolyzed, releasing carmustine, carboxyphenoxypropane, and sebacic acid into the surrounding brain tissue.

12.3 Pharmacokinetics

Carmustine concentrations delivered by GLIADEL Wafer in human brain tissue have not been determined. Following wafer insertion, the mean whole blood Cmax(± SD) is 10.2 ng/mL ± 4.8 ng/mL.

Absorption

Systemic absorption of carmustine is measurable for approximately 24 hours after wafer insertion. Carmustine Cmaxwas reached approximately 3 hours after wafer insertion.

Elimination

Metabolism

Carmustine degrades both spontaneously and metabolically.

12.6 Wafer Biodegradation

GLIADEL Wafers are biodegradable when implanted into the human brain. Wafer remnants were visible on CT scans obtained 49 days after implantation of GLIADEL Wafer. More than 70% of the copolymer degrades within three weeks. Wafer remnants have been present at re-operation and autopsy up to 7.8 months after GLIADEL Wafer implantation and consisted mostly of water and monomeric components with minimal detectable carmustine present.

13 NONCLINICAL TOXICOLOGY

13.1 Carcinogenesis, Mutagenesis, Impairment of Fertility

No carcinogenicity, mutagenicity, or impairment of fertility studies have been conducted with GLIADEL Wafer. Carcinogenicity, mutagenicity, and impairment of fertility studies have been conducted with carmustine, the active component of GLIADEL Wafer. Carmustine was carcinogenic in rats and mice when delivered by intraperitoneal injection at doses lower than those delivered by GLIADEL Wafer at the recommended dose. There were increases in tumor incidence in all treated animals. Carmustine was mutagenic in vitro (Ames assay, human lymphoblast HGPRT assay) and clastogenic both in vitro (V79 hamster cell micronucleus assay) and in vivo (SCE assay in rodent brain tumors, mouse bone marrow micronucleus assay).

In male rats carmustine caused testicular degeneration at intraperitoneal doses of 8 mg/kg/week for eight weeks (about 1.3 times the recommended human dose based on body surface area).

14 CLINICAL STUDIES

14.1 Newly-Diagnosed High-Grade Glioma

Study 1 was a multicenter, double-blind, placebo-controlled, clinical trial in adult patients with newly-diagnosed high-grade glioma. A total of 240 patients were randomized (1:1) to receive up to eight GLIADEL Wafers or matched placebo wafers following maximal tumor resection. Patients received post-operative radiation therapy (55-60 Gy delivered in 28 to 30 fractions over six weeks) starting three weeks after surgery. Patients with anaplastic oligodendroglioma also received systemic chemotherapy (6 cycles of PCV- lomustine 110 mg/m^2day 1, procarbazine 60 mg/m^2days 8-21, vincristine 1.4 mg/m^2days 8 and 29).

The population in Study 1 was 67% male and 97% White, and the median age was 53 years (range: 21-72). Eighty-seven percent had a Karnofsky performance status ≥ 70% and 71% had a Karnofsky performance status of ≥ 80%. Seventy-eight percent had a histologic subtype of glioblastoma as determined by central pathology review. Thirty-eight percent of patients received 8 wafers and 78% received ≥ 6 wafers. Starting three weeks after surgery, 80% of patients received standard limited field radiation therapy (RT) described as 55-60 Gy delivered in 28 to 30 fractions over six weeks; 11% received no radiotherapy and the remainder received non-standard radiotherapy or a combination of standard and non-standard radiotherapy. At the time of progression, 12% received systemic chemotherapy. Patients were followed for at least three years or until death.

Efficacy results for patients randomized in Study 1 are summarized in Table 6 and Figure 6. Overall survival among all patients with newly diagnosed high-grade glioma, the primary outcome measure, was prolonged in the GLIADEL arm. Overall survival in the subset of patients with glioblastoma, a secondary outcome measure, was not significantly prolonged.

Table 6. Overall Survival in Patients with Newly-Diagnosed High-Grade Glioma, Study 1.
Overall Survival – ITT [Based on a post-final analysis, protocol specified non-stratified log-rank test.] | Gliadel Wafer (n=120) | Placebo Wafer (n=120)
Number of deaths, n (%) | 111 (93%) | 117(98%)
Median overall survival, months (95% CI) | 13.9 (12.1, 15.1) | 11.6 (10.2, 12.7)
Hazard ratio (95% CI) | 0.73 (0.56, 0.95)
Log-Rank test p-value | <0.02 [p-value not adjusted for multiple comparisons]

Figure 6: Kaplan-Meier Curves of Overall Survival in Patients with Newly Diagnosed High-Grade Glioma, Study 1. [Based on a post-final analysis, protocol specified non-stratified log-rank test; p-value not adjusted for multiple comparisons]

14.2 Recurrent Glioblastoma

Study 2 was a multicenter, double-blind, placebo controlled, clinical trial in adult patients with recurrent high-grade glioma. Patients were required to have had prior definitive external beam radiation therapy sufficient to disqualify them from additional radiation therapy. Following maximal tumor resection and confirmation of high-grade glioma, a total of 222 patients were randomized (1:1) to receive a maximum of eight GLIADEL Wafers (n=110) or matched placebo wafers (n=112) positioned to cover the entire resection surface. All patients were eligible to receive chemotherapy which was withheld at least four weeks (six weeks for nitrosoureas) prior to and two weeks after surgery. Patients were followed for up to 71 months.

The population in Study 2 was 64% male and 92% White, and the median age was 49 years (range: 19-80). Sixty-five percent had a histologic subtype of glioblastoma, 26% had anaplastic astrocytoma or another anaplastic variant, 73% had a Karnofsky performance status ≥ 70, 53% had a Karnofsky performance status of ≥ 80%, 73% had only one prior surgery, and 46% had prior treatment with nitrosourea. Eighty-one percent of patients received 8 wafers and 96% received ≥ 6 wafers.

Survival and 6-month mortality rate in the subgroup of patients with recurrent glioblastoma, were exploratory outcome measures and are summarized in Table 7 and Figures 7 and 8. No survival prolongation was observed in patients with pathologic diagnoses other than glioblastoma.

Table 7. Main Efficacy Outcome Measures in Patients with Recurrent Glioblastoma, Study 2.
 | GLIADEL Wafer | Placebo Wafer
GLIOBLASTOMA | n=72 | n=73
6-Month Survival
Number of deaths, n (%) | 32 | 47
6-month survival rate (%) | 56% | 36%
Log-Rank test p-value Gehan's generalized Wilcoxon Test p-value | 0.013 [p-value not adjusted for multiple comparisons] 0.015
Overall Survival
Number of deaths, n (%) | 71 (99%) | 72 (99%)
Median overall survival (95% CI (months) | 6.51 (5.32, 7.49) | 4.63 (3.78, 5.52)
Log-Rank test p-value Gehan's generalized Wilcoxon Test p-value | 0.181 0.021

Figure 7: Kaplan-Meier Curves of 6-Month Survival for Patients with Recurrent Glioblastoma, Study 2.

Figure 8: Kaplan-Meier Curves of Overall Survival for Patients with Recurrent Glioblastoma, Study 2.

15 REFERENCES

1. "OSHA Hazardous Drugs". OSHA.http://www.osha.gov/SLTC/hazardousdrugs/index.html

16 HOW SUPPLIED/STORAGE AND HANDLING

GLIADEL Wafer is supplied in a single dose treatment box containing eight individually pouched wafers. Each wafer contains 7.7 mg of carmustine and is packaged in two aluminum foil laminate pouches. The inner pouch is sterile and is designed to maintain product sterility and protect the product from moisture. The outer pouch is a peelable overwrap. The outside surface of the outer pouch is not sterile.

NDC for single dose treatment box: 24338-050-08

STORAGE AND HANDLING

Store GLIADEL Wafer at or below -20ºC (-4ºF).

Do not keep unopened foil pouches at ambient room temperature for more than six hours at a time for up to three cycles within a 30-day period.

GLIADEL Wafer is a cytotoxic drug and special handling and disposal procedures should be considered.^1

17 PATIENT COUNSELING INFORMATION

Seizures

Advise patients to report any new or change in their seizure activity [see Warnings and Precautions (5.1)] .

Intracranial Hypertension

Advise patients to report severe headaches, nausea, vomiting or new onset visual disturbances [see Warnings and Precautions (5.2)] .

Impaired Neurosurgical Wound Healing

Advise patients to report any evidence of wound dehiscence, fever or cerebrospinal fluid leak [see Warnings and Precautions (5.3)].

Meningitis

Advise patients to report symptoms of meningitis such as fever or stiff neck [see Warnings and Precautions (5.4)].

Embryo-Fetal Toxicity

Advise patients of the potential risk to a fetus. Advise women to inform their healthcare provider of a known or suspected pregnancy [see Warnings and Precautions (5.6), Use in Specific Populations (8.1)] .

Advise females of reproductive potential to use effective contraception for at least 6 months after implantation of GLIADEL Wafer [see Use in Specific Populations (8.3)] .

Advise males with female partners of reproductive potential to use effective contraception for 3 months following implantation of GLIADEL Wafer [see Use in Specific Populations (8.3), Nonclinical Toxicology (13.1)] .

Lactation

Advise women not to breastfeed following implantation with GLIADEL Wafers and for at least 7 days after implantation [see Use in Specific Populations (8.2)] .

Infertility

Advise males of reproductive potential that GLIADEL Wafer may impair fertility [see Use in Specific Populations (8.3), Nonclinical Toxicology (13.1)] .

Manufactured by
Eisai Inc.
Nutley, NJ 07110

Distributed by
Azurity Pharmaceuticals, Inc.
Woburn, MA 01801

Patent: https://azurity.com/patents

GLIADEL®is a registered trademark of Eisai Inc.

GL-PI-05

PRINCIPAL DISPLAY PANEL - 8 Wafer Box

NDC 24338-050-08

GLIADEL®WAFER
(carmustine implant)

7.7 mg carmustine/wafer

For intracranial use.

Each sterile wafer contains
192.3 mg polifeprosan 20 and
7.7 mg carmustine.

Contents:
8 wafers, individually packaged

Store at or below -20°C (-4°F).
Rx only

Warning:Cytotoxic agent
See package insert for full prescribing information.
Keep out of the reach of children.

Azurity PHARMACEUTICALS, Inc.